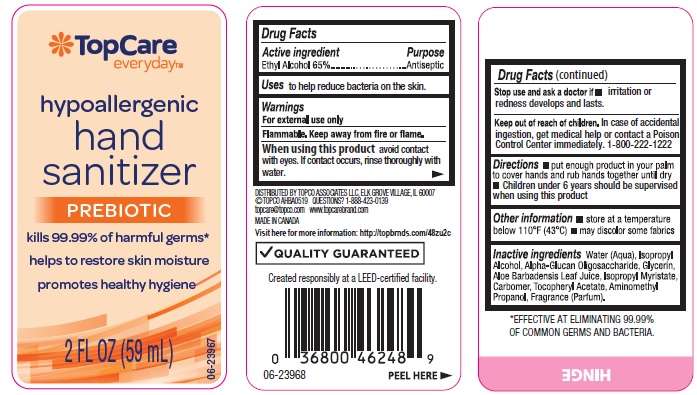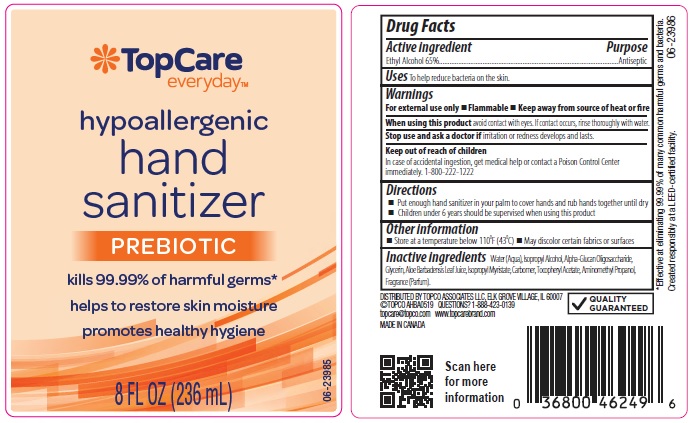 DRUG LABEL: TopCare Prebiotic Hand Sanitizer
NDC: 36800-996 | Form: LIQUID
Manufacturer: TopCo Associates LLC
Category: otc | Type: HUMAN OTC DRUG LABEL
Date: 20190821

ACTIVE INGREDIENTS: ALCOHOL 650 mg/1 mL
INACTIVE INGREDIENTS: WATER; ISOPROPYL ALCOHOL; .ALPHA.-GLUCAN OLIGOSACCHARIDE; GLYCERIN; ALOE VERA LEAF; ISOPROPYL MYRISTATE; CARBOMER 934; .ALPHA.-TOCOPHEROL ACETATE, DL-; AMINOMETHYLPROPANOL

Drug Facts

Active ingredient

Ethyl Alcohol 65%

Purpose

Antiseptic

Uses

to help reduce bacteria on the skin

Warnings

For external use only

- Flammable
- Keep away from source of heat or fire

When using this product

avoid contact with eyes. If contact occurs, rinse thoroughly with water.

Stop use and ask a doctor if

irritation or redness develops and lasts

Keep out of reach of children.

In case of accidental ingestion, get medical help or contact a Poison Control Center immediately. 1-800-222-1222

Directions

- put enough hand sanitizer in your palm to cover hands and rub hands together until dry.
- children under 6 years should be supervised when using this product.

Other information

- store at a temperature below 110°F (43°C)
- may discolor certain fabrics or surfaces

Inactive ingredients

Water (Aqua), Isopropyl Alcohol, Alpha-Glucan Oligosaccharide, Glycerin, Aloe Barbadensis Leaf Juice, Isopropyl Myristate, Carbomer, Tocopheryl Acetate, Aminomethyl Propanol, Fragrance (Parfum).